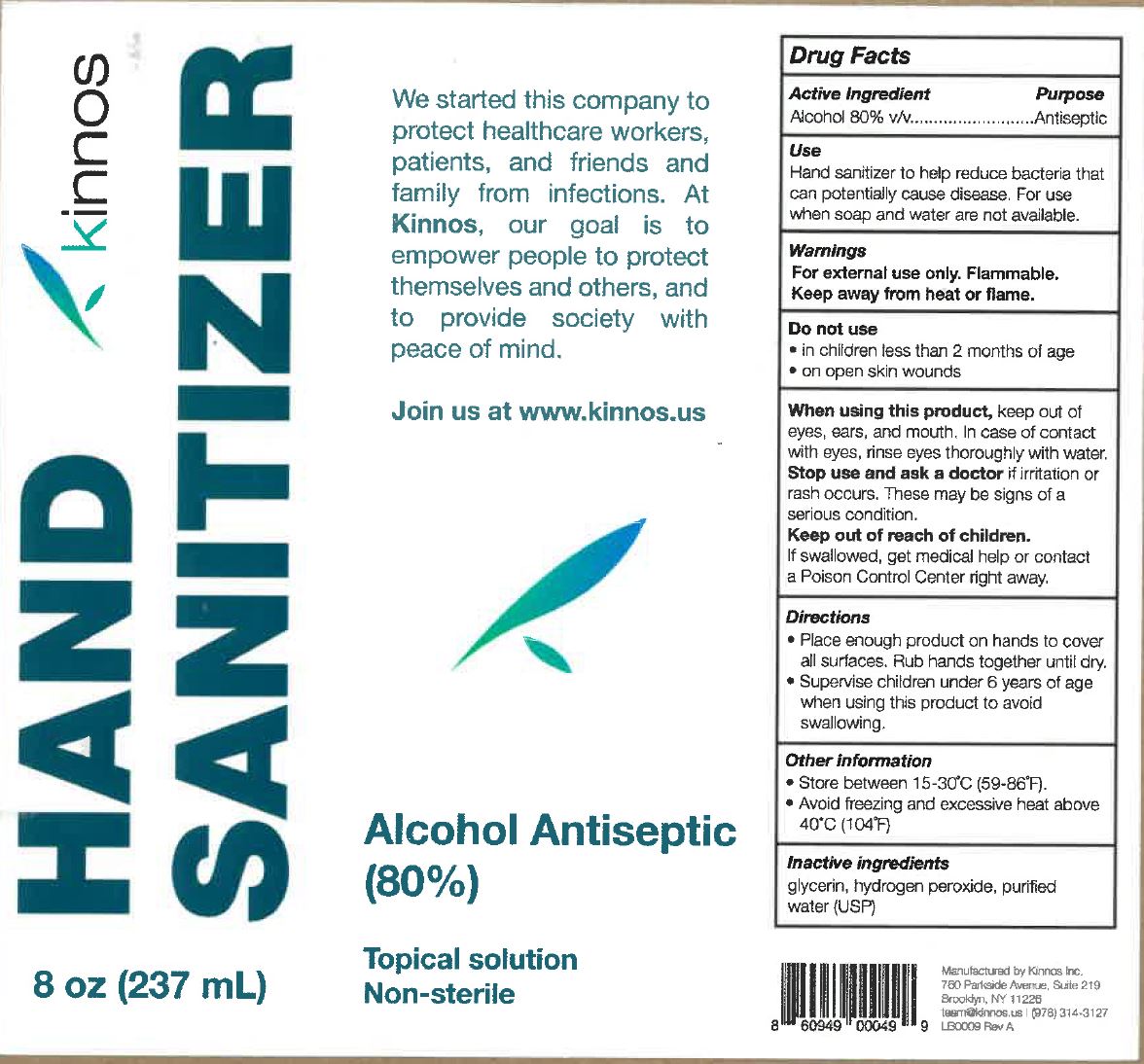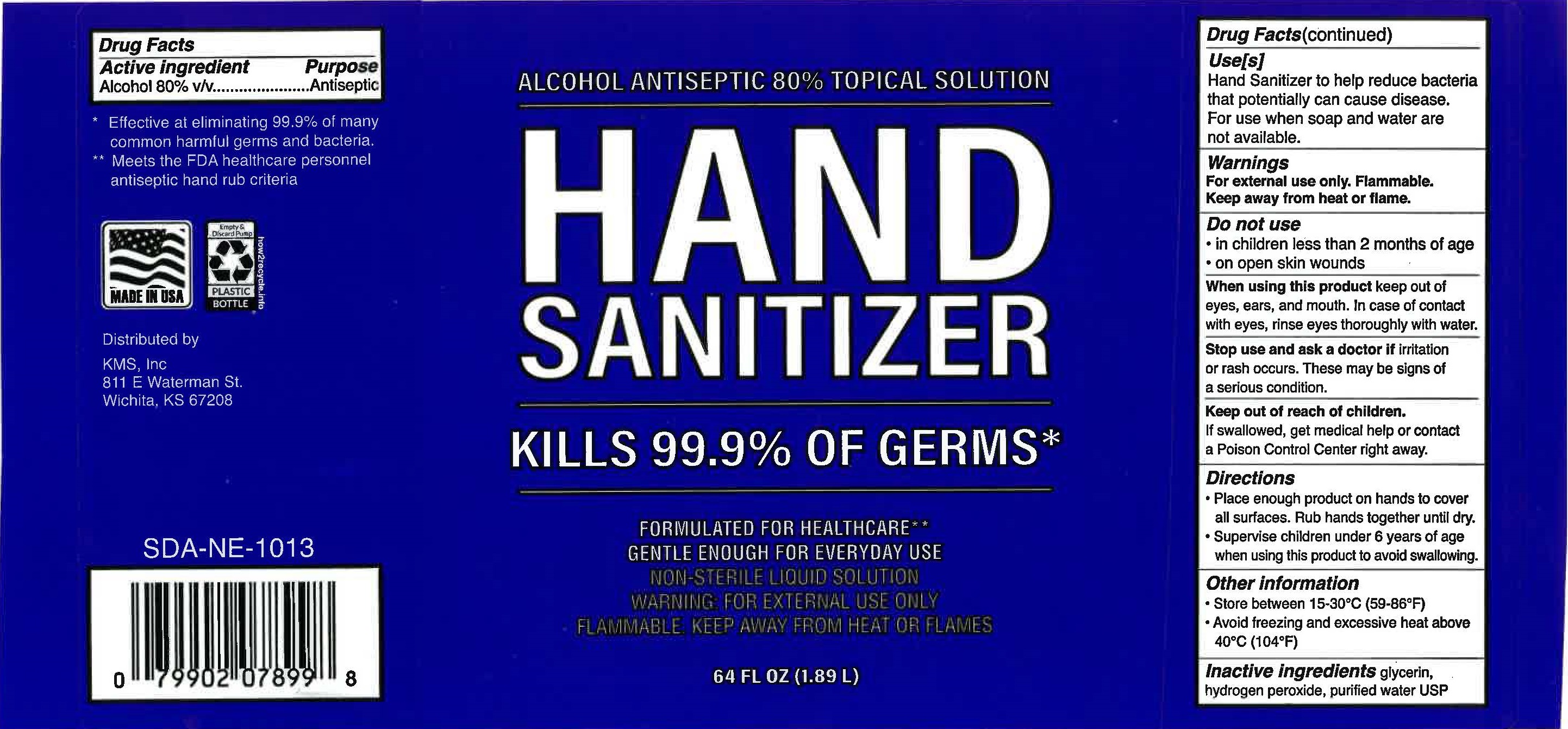 DRUG LABEL: 80% Alcohol Hand Sanitizer
NDC: 73956-301 | Form: SOLUTION
Manufacturer: Phoenix Products Company
Category: otc | Type: HUMAN OTC DRUG LABEL
Date: 20200601

ACTIVE INGREDIENTS: ALCOHOL 80 mL/100 mL
INACTIVE INGREDIENTS: GLYCERIN 1.45 mL/100 mL; HYDROGEN PEROXIDE 0.125 mL/100 mL; WATER 18.42 mL/100 mL

This is a hand rub manufactured according to the Temporary Policy for Preparation of Certain Alcohol-Based Hand Rub Products During the Public Health Emergency (CoViD-19); Guidance for Industry.

The hand rub is manufactured using only the following United States Pharmacopoeia (USP) grade ingredients in the preparation of the product (percentage in final product formulation) consistent with World Health Organization (WHO) recommendations:

1. Alcohol (ethanol) (USP or Food Chemical Codex (FCC) grade) (80%, volume/volume (v/v)) in an aqueous solution denatured according to Alcohol and Tobacco Tax and Trade Bureau regulations in 27 CFR part 20.
2. Glycerol (1.45% v/v).
3. Hydrogen peroxide (0.125% v/v).
4. Sterile distilled water or boiled cold water.

The firm does not add other active or inactive ingredients. Different or additional ingredients may impact the quality and potency of the product.

Active Ingredient(s)

Alcohol 80% v/v. Purpose: Antiseptic

Purpose

Antiseptic, Hand Rub

Use

Health care personnel hand rub to help reduce bacteria that potentially can cause disease.

Warnings

For external use only. Flammable. Keep away from heat or flame

Do not use

- in children less than 2 months of age
- on open skin wounds

When using this product keep out of eyes, ears, and mouth. In case of contact with eyes, rinse eyes thoroughly with water.

Stop use and ask a doctor if irritation or rash occurs. These may be signs of a serious condition.

Keep out of reach of children. If swallowed, get medical help or contact a Poison Control Center right away.

Directions

- Place enough product on hands to cover all surfaces. Rub hands together until dry.
- Supervise children under 6 years of age when using this product to avoid swallowing.

Other information

- Store between 15-30C (59-86F)
- Avoid freezing and excessive heat above 40C (104F)

Inactive ingredients

glycerin, hydrogen peroxide, purified water USP

Package Label - Principal Display Panel

KMS

* Effective at eliminating 99.9% of many

common harmful germs and bacteria.

** Meets the FDA healthcare personnel

antiseptic hand rub criteria

Made in USA

Empty &

Discard Pump

PLASTIC BOTTLE

how2recycle.info

Distributed by

KMS, Inc.

811 E Waterman St.

Wichita, KS 67208

SDA-NE-1013

0 79902 07899 8

ALCOHOL ANTISEPTIC 80 % TOPICAL SOLUTION

HAND
SANITIZER

KILLS 99.9% OF GERMS*

FORMULATED FOR HEALTHCARE**

GENTLE ENOUGH FOR EVERYDAY USE

NON-STERILE LIQUID SOLUTION

WARNING FOR EXTERNAL USE ONLY

FLAMMABLE. KEEP AWAY FROM HEAT OR FLAMES

64 FL OZ (1.89 L)

Package Label - Principal Display Panel

[Kinnos 8 oz]

kinnos

HAND SANITIZER

8 oz (237mL)

We started this company to
protect healthcare workers,
patients, and friends and
family from infections. At
Kinnos, our goal is to
empower people to protect
themselves and others, and
to provide society with
peace of mind.

Join us at www.kinnos.us

Alcohol Antiseptic
(80%)
Topical solution
Non-sterile

Manufactured by Kinnos Inc.

760 Parkside Avenue, Suite 219

Brooklyn, NY 11226

team@kinnos.us | (978) 314-3127

LB0009 Rev A

8 60949 00049 9